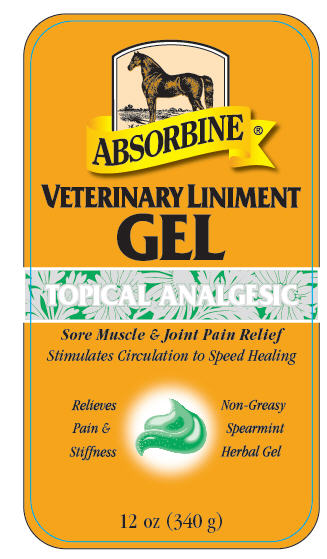 DRUG LABEL: Absorbine Veterinary
NDC: 11444-075 | Form: GEL
Manufacturer: W. F. Young, Inc.
Category: animal | Type: OTC ANIMAL DRUG LABEL
Date: 20241101

ACTIVE INGREDIENTS: MENTHOL, UNSPECIFIED FORM 4 g/100 g

VETERINARY LINIMENT
GEL
TOPICAL ANALGESIC

DESCRIPTION

Absorbine® Veterinary Liniment Gel Helps Your Horse to Heal Itself.

Liniments are mild stimulants to the circulatory system that hasten and assist nature in returning a fatigued muscle, joint or tendon to normal. Absorbine Liniment Gel combines the same time honored blend of Calendula, Echinacea and Wormwood herbs as our trusted Absorbine® Veterinary Liniment.

INDICATIONS

Veterinary Liniment Gel relieves the pain and swelling of joints and muscles due to minor injuries, over exertion and arthritis.

DIRECTIONS FOR USE

LEGS

To relieve pain and reduce swelling of the legs, rub Absorbine Gel in thoroughly three or more times a day. To speed effectiveness, apply gel with the lay of the hair and lightly wrap. Absorbine Gel is also effective for pre-workout rubs and post-workout "set up" wraps.

BACK, SHOULDER, AND FLANK

For relief of soreness and stiffness, rub Absorbine Gel in thoroughly. Apply three or more times a day. Do not apply Gel under the saddle area if you're going to ride the horse after treatment.

SHIPPING

During transportation, many horses injure their lower legs in the trailer or they "stock up " from prolonged standing. Shipping wraps are recommended to prevent injuries and Absorbine Gel is safe and effective under porous wraps in reducing swelling.

ARTHRITIS

A common condition in older horses, Absorbine Gel helps to loosen stiff, arthritic joints and reduce the swelling.

ACTIVE INGREDIENTS

Natural Menthol 4%. Also Contains: Alcohol 53%.

CAUTION

Use only as directed. For external use only. Keep out of reach of children. Avoid contact with eyes and mucous membranes. If skin irritation develops or symptoms persist for more than 10 days, discontinue use. For severe injuries, consult a veterinarian. For animal use only.

WARNING

Flammable. Keep away from fire, sparks and heated surfaces. Store at room temperature.

Distributed by: W. F. Young, Inc.
302 Benton Drive
E. Longmeadow, MA 01028 USA
©WFY

www.absorbine.com

RM 342489B

PRINCIPAL DISPLAY PANEL - 340 g Label

ABSORBINE®

VETERINARY LINIMENT
GEL

TOPICAL ANALGESIC

Sore Muscle & Joint Pain Relief

Stimulates Circulation to Speed Healing

Relieves
Pain &
Stiffness

Non-Greasy
Spearmint
Herbal Gel

12 oz (340 g)